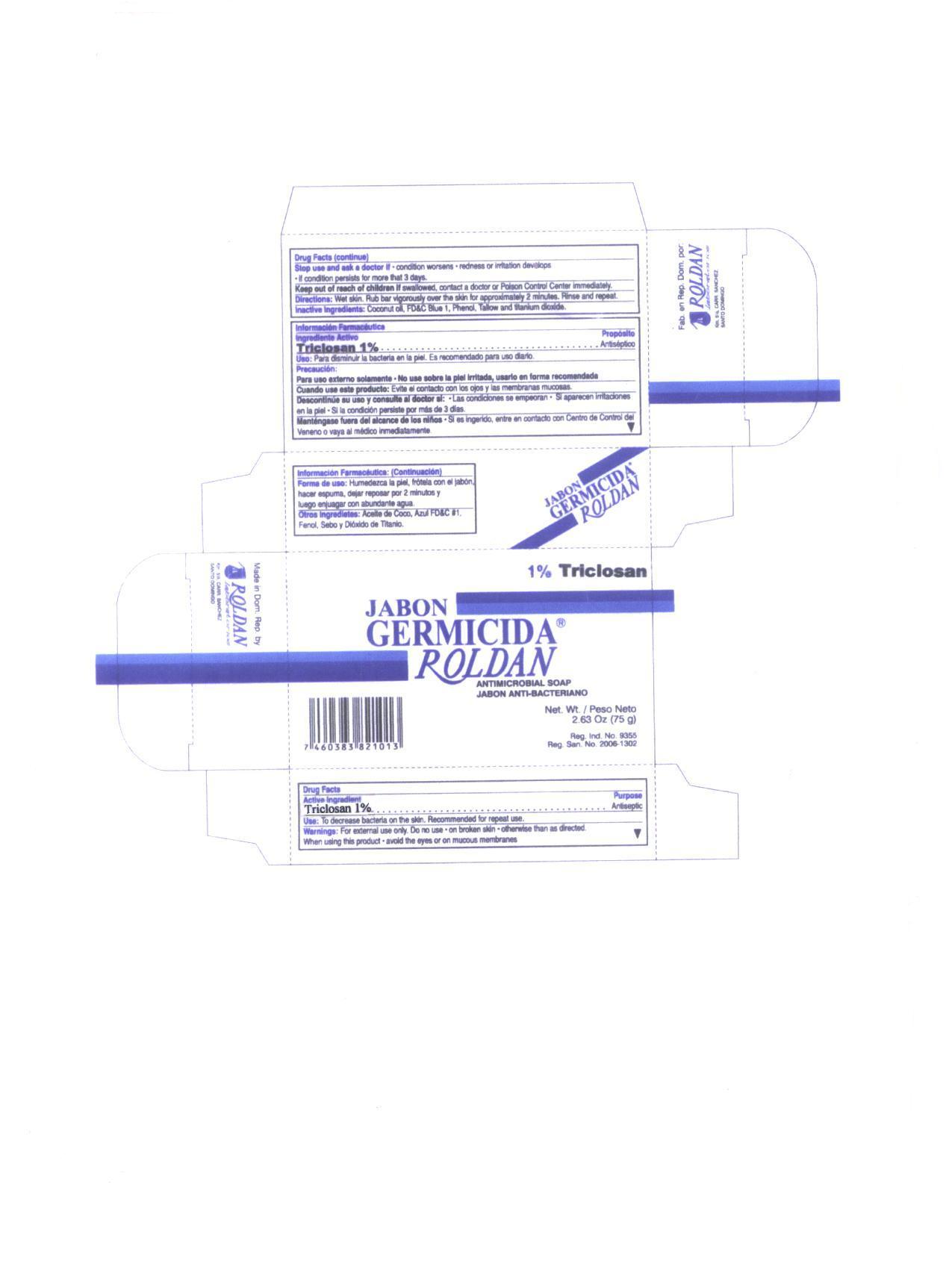 DRUG LABEL: Germicida
NDC: 66449-003 | Form: SOAP
Manufacturer: Laboratorios Roldan, S.A.
Category: otc | Type: HUMAN OTC DRUG LABEL
Date: 20120612

ACTIVE INGREDIENTS: TRICLOSAN 1.0 g/100 g
INACTIVE INGREDIENTS: COCONUT OIL; FD&C BLUE NO. 1; PHENOL; BEEF TALLOW; TITANIUM DIOXIDE

Drug Facts

Active Ingredient
Triclosan 1%

Purpose
Antiseptic

INDICATIONS AND USAGE

Use To decrease bacteria on the skin. Recommended for repeated use.

WARNINGS

Warnings For external use only. Do not use • on broken skin • otherwise than as directed.

When using this product • avoid with eyes or on mucous membranes

Stop use and ask a doctor if • condition worsens • irritation or redness develops • if condition persists for more than 3 days

KEEP OUT OF REACH OF CHILDREN

Keep out of the reach of children. If swallowed contact a doctor or Poison Control Center immediately.

DOSAGE AND ADMINISTRATION

Directions Wet skin. Rub bar vigorously over the skin for approximately 2 minutes. Rinse and repeat.

INACTIVE INGREDIENT

Inactive ingredients Coconut Oil, FDC Blue 1, Phenol, Tallow and titanium dioxide

Package Label